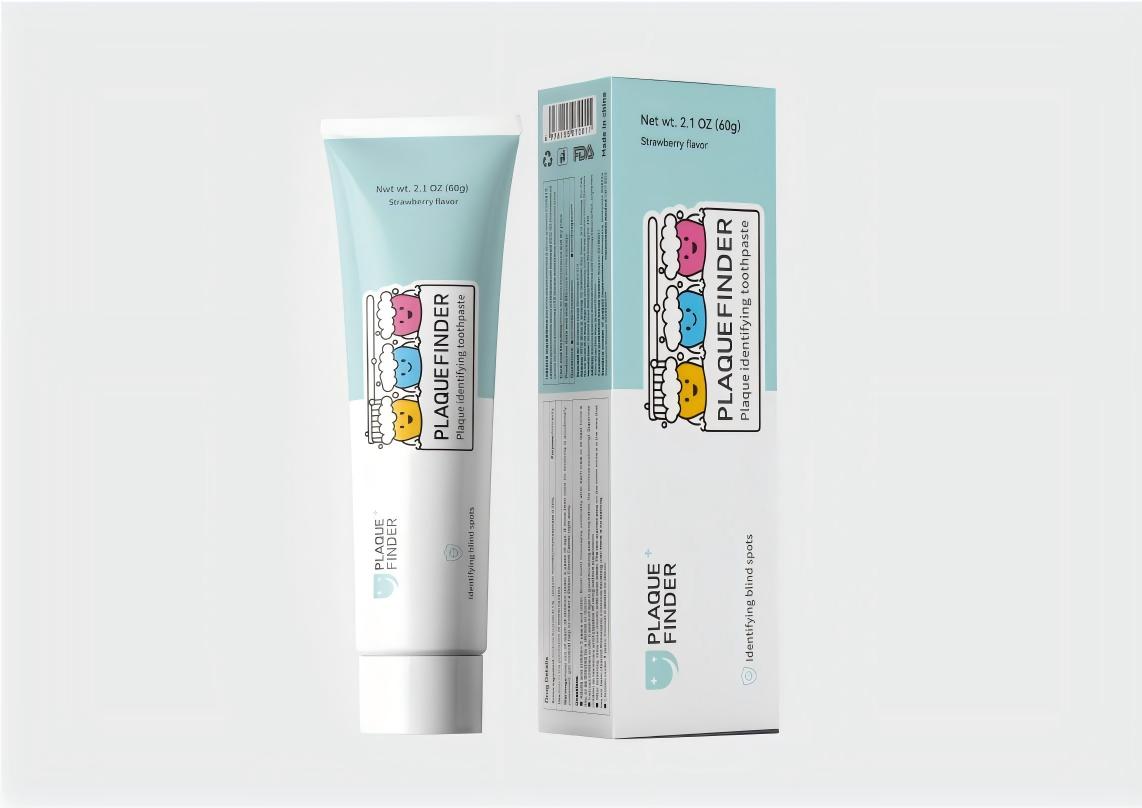 DRUG LABEL: Plaque identifying
NDC: 85869-123 | Form: POWDER, DENTIFRICE
Manufacturer: Shenzhen Yagao Technology Co., Ltd.
Category: homeopathic | Type: HUMAN OTC DRUG LABEL
Date: 20250619

ACTIVE INGREDIENTS: WATER 1 g/1 g; SORBITOL 1 g/1 g
INACTIVE INGREDIENTS: CI 45410; HYDRATED SILICA; SODIUM LAURYL SULFATE; FLAVOR SPICE MINT N&A110589; POLYGLYCERYL-10 LAURATE; SUCRALOSE; GLYCERIN; PEG-40 LANOLIN; XANTHAN GUM; SODIUM BENZOATE; ACESULFAME POTASSIUM

INACTIVE INGREDIENT

hydrated silica,glycerin,CI 45410,xanthan gum,sodium lauryl sulfate,sodium benzoate,flavor,polyglyceryl-10 laurate,acesulfame potassium,sucralose

PURPOSE

Clean your teeth

DOSAGE AND ADMINISTRATION

60g

WARNINGS

Do not swallow directly

ACTIVE INGREDIENT

sorbitol,water

KEEP OUT OF REACH OF CHILDREN SECTION

INDICATIONS AND USAGE

Apply directly to a toothbrush to clean your mouth